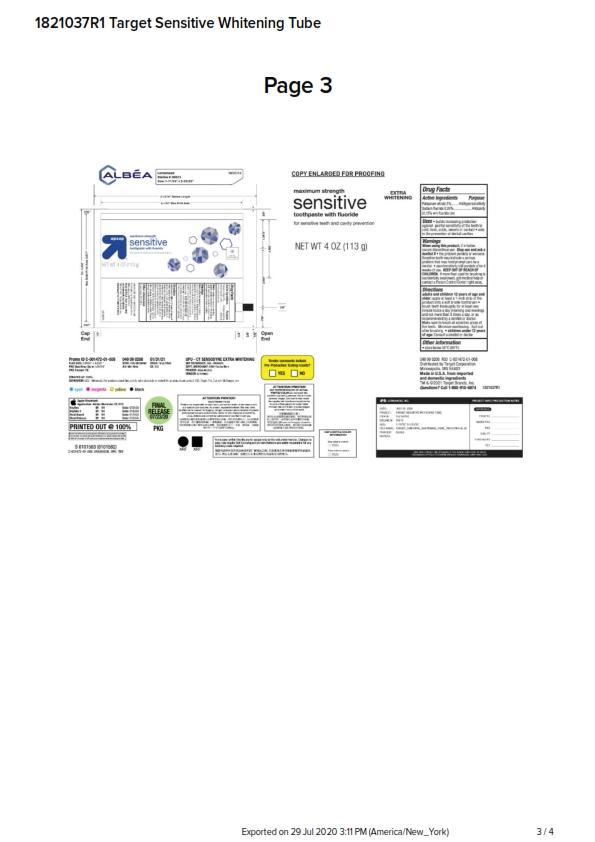 DRUG LABEL: Target Sensitive Whitening TP
NDC: 11673-237 | Form: PASTE, DENTIFRICE
Manufacturer: Target
Category: otc | Type: HUMAN OTC DRUG LABEL
Date: 20251114

ACTIVE INGREDIENTS: POTASSIUM NITRATE 5 g/100 g; SODIUM FLUORIDE 0.24 g/100 g
INACTIVE INGREDIENTS: HYDRATED SILICA; WATER; SORBITOL; COCAMIDOPROPYL BETAINE; SACCHARIN SODIUM; SODIUM TRIPOLYPHOSPHATE ANHYDROUS; POLYETHYLENE GLYCOL 400; TITANIUM DIOXIDE; SODIUM HYDROXIDE; GLYCERIN; XANTHAN GUM; SODIUM METHYL COCOYL TAURATE

5820081 Target Sensitive Whitening TP (8015201)

ACTIVE INGREDIENT

Potassium nitrate 5%

Sodium fluoride 0.24% (0.15% w/v fluoride ion)

PURPOSE

Antihypersensitivity

Anticavity

INDICATIONS AND USAGE

builds increasing protection against painful sensitivity of the teeth to cold, heat, acids, sweets or contact * aids in the prevention of dental cavities

When using this product, if irritation occurs discontinue use. Stop use and ask a doctor if * the problem persists or worsens. Sensitive teeth may indicate a serious problem that may need prompt care by a dentist. * pain/sensitivity still persists after 4 weeks of use.

KEEP OUT OF REACH OF CHILDREN. If more than is used for brushing is accidentally swallowed, get medical help or contact a Poison Control Center right away.

DOSAGE AND ADMINISTRATION

adults and children 12 years of age and older: apply at least a 1-inch strip of the product onto a soft bristle toothbrush * brush teeth thoroughly for at least one minute twice a day (morning and evening), and not more than 3 times a day, or as recommended by a dentist or doctor. Make sure to brush all sensitive areas of the teeth. Minimize swallowing. Spit out after brushing. * children under 12 years of age: Consult a dentist or doctor.

OTHER SAFETY INFORMATION

store below 30C (86F)

INACTIVE INGREDIENT

water, sorbitol, hydrated silica, glycerin, pentasodium triphosphate, PEG-8, flavor, titanium dioxide, sodium methyl cocoyl taurate, cocomidopropyl betaine, xanthan gum, sodium hydroxide, sodium saccharin